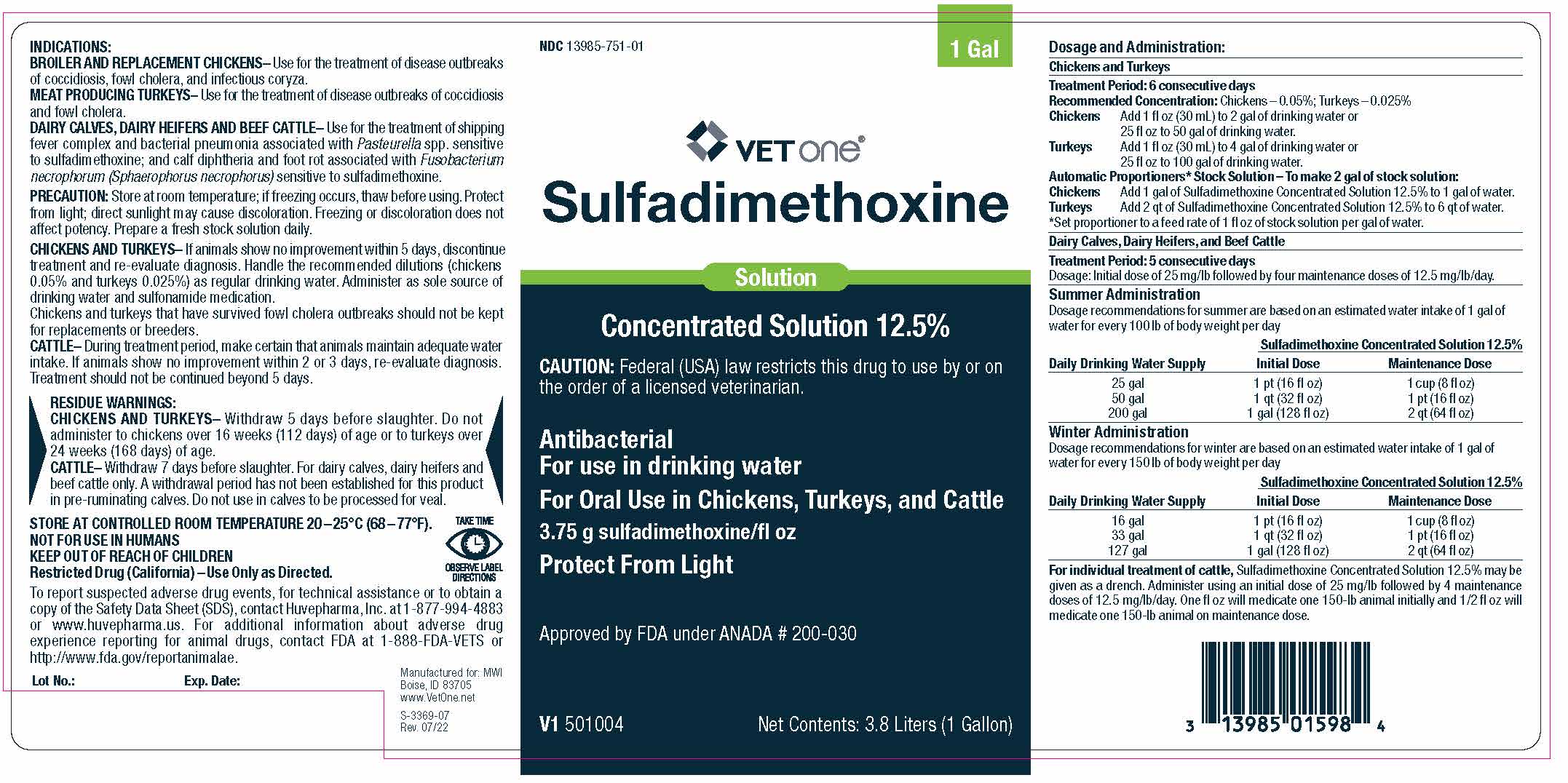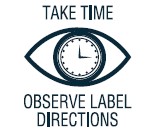 DRUG LABEL: Sulfadimethoxine 
NDC: 13985-751 | Form: SOLUTION, CONCENTRATE
Manufacturer: MWI Veterinary Supply, Inc.
Category: animal | Type: PRESCRIPTION ANIMAL DRUG LABEL
Date: 20230605

ACTIVE INGREDIENTS: Sulfadimethoxine 3750 mg/0.2366 L

Sulfadimethoxine

Solution

Concentrated Solution 12.5%

CAUTION: Federal (USA) law restricts this drug to use by or on the order of a licensed veterinarian.

Antibacterial

For use in drinking water

For Oral Use in Chickens, Turkeys, and Cattle

3.75 g sulfadimethoxine/fl oz

Protect From Light

Approved by FDA under ANADA # 200-030

Net Contents: 3.8 Liters (1 Gallon)

INDICATIONS:
BROILER AND REPLACEMENT CHICKENS– Use for the treatment of disease outbreaks of coccidiosis, fowl cholera, and infectious coryza.
MEAT PRODUCING TURKEYS– Use for the treatment of disease outbreaks of coccidiosis and fowl cholera.
DAIRY CALVES, DAIRY HEIFERS AND BEEF CATTLE– Use for the treatment of shipping fever complex and bacterial pneumonia associated with Pasteurella spp. sensitive to sulfadimethoxine; and calf diphtheria and foot rot associated with Fusobacterium necrophorum (Sphaerophorus necrophorus) sensitive to sulfadimethoxine.

GENERAL PRECAUTIONS

PRECAUTION: Store at room temperature; if freezing occurs, thaw before using. Protect from light; direct sunlight may cause discoloration. Freezing or discoloration does not affect potency. Prepare a fresh stock solution daily.

CHICKENS AND TURKEYS– If animals show no improvement within 5 days, discontinue treatment and re-evaluate diagnosis. Handle the recommended dilutions (chickens 0.05% and turkeys 0.025%) as regular drinking water. Administer as sole source of drinking water and sulfonamide medication.
Chickens and turkeys that have survived fowl cholera outbreaks should not be kept for replacements or breeders.
CATTLE– During treatment period, make certain that animals maintain adequate water intake. If animals show no improvement within 2 or 3 days, re-evaluate diagnosis. Treatment should not be continued beyond 5 days.

RESIDUE WARNINGS:
CHICKENS AND TURKEYS- Withdraw 5 days before slaughter. Do not administer to chickens over 16 weeks (112 days) of age or to turkeys over 24 weeks (168 days) of age.
CATTLE- Withdraw 7 days before slaughter. For dairy calves, dairy heifers and beef cattle only. A withdrawal period has not been established for this product in pre-ruminating calves. Do not use in calves to be processed for veal.

STORAGE AND HANDLING

STORE AT CONTROLLED ROOM TEMPERATURE 20 – 25°C (68 – 77°F).

USER SAFETY WARNINGS

NOT FOR USE IN HUMANS
KEEP OUT OF REACH OF CHILDREN
Restricted Drug (California) – Use Only as Directed.

ADVERSE REACTIONS

To report suspected adverse drug events, for technical assistance or to obtain a copy of the Safety Data Sheet (SDS), contact Huvepharma, Inc. at 1-877-994-4883 or www.huvepharma.us. For additional information about adverse drug experience reporting for animal drugs, contact FDA at 1-888-FDA-VETS or http://www.fda.gov/reportanimalae.

Lot No.: Exp. Date: Manufactured for: MWI
Boise, ID 83705
www.VetOne.net

Dosage and Administration:

Chickens and Turkeys

Treatment Period: 6 consecutive days

Recommended Concentration: Chickens – 0.05%; Turkeys – 0.025%

Chickens

Add 1 fl oz (30 mL) to 2 gal of drinking water or 25 fl oz to 50 gal of drinking water.

Turkeys

Add 1 fl oz (30 mL) to 4 gal of drinking water or 25 fl oz to 100 gal of drinking water.

Automatic Proportioners *Stock Solution – To make 2 gal of stock solution:

Chickens

Add 1 gal of Sulfadimethoxine Concentrated Solution 12.5% to 1 gal of water.

Turkeys

Add 2 qt of Sulfadimethoxine Concentrated Solution 12.5% to 6 qt of water.

*Set proportioner to a feed rate of 1 fl oz of stock solution per gal of water.

Dairy Calves, Dairy Heifers, and Beef Cattle

Treatment Period: 5 consecutive days

Dosage: Initial dose of 25 mg/lb followed by four maintenance doses of 12.5 mg/lb/day. Summer Administration

Dosage recommendations for summer are based on an estimated water intake of 1 gal of water for every 100 lb of body weight per day.

Sulfadimethoxine Concentrated Solution 12.5%

Daily Drinking Water Supply

Initial Dose

Maintenance Dose

25 gal

1 pt (16 fl oz)

1 cup (8 fl oz)

50 gal

1 qt (32 fl oz)

1 pt (16 fl oz)

200 gal

1 gal (128 fl oz)

2 qt (64 fl oz)

Winter Administration

Dosage recommendations for winter are based on an estimated water intake of 1 gal of water for every 150 lb of body weight per day

Sulfadimethoxine Concentrated Solution 12.5%

Daily Drinking Water Supply

Initial Dose

Maintenance Dose

16 gal

1 pt (16 fl oz)

1 cup (8 fl oz)

33 gal

1 qt (32 fl oz)

1 pt (16 fl oz)

127 gal

1 gal (128 fl oz)

2 qt (64 fl oz)

For individual treatment of cattle, Sulfadimethoxine Concentrated Solution 12.5% may be given as a drench. Administer using an initial dose of 25 mg/lb followed by 4 maintenance doses of 12.5 mg/lb/day. One fl oz will medicate one 150-lb animal initially and ½ fl oz will medicate one 150-lb animal on maintenance dose.